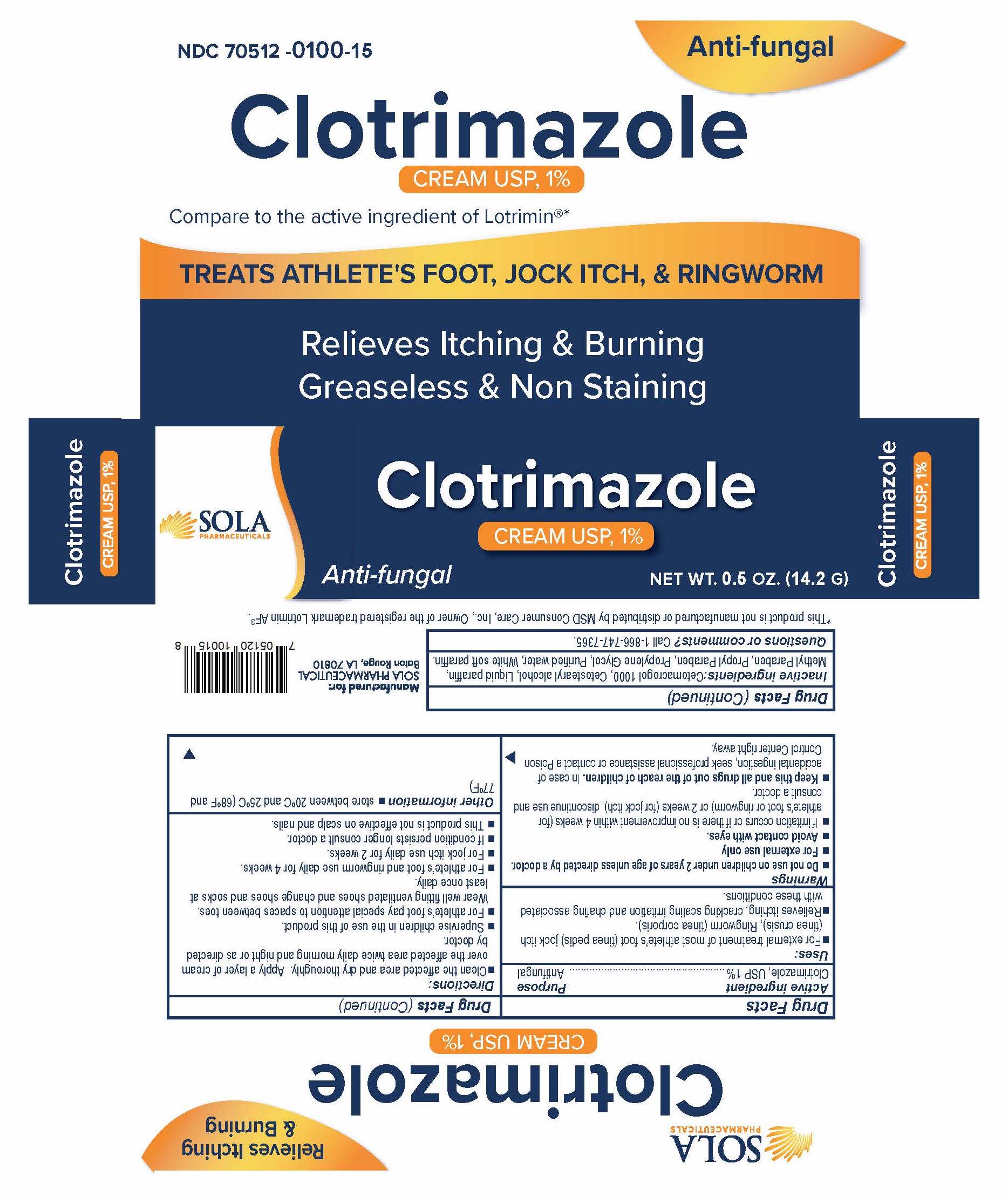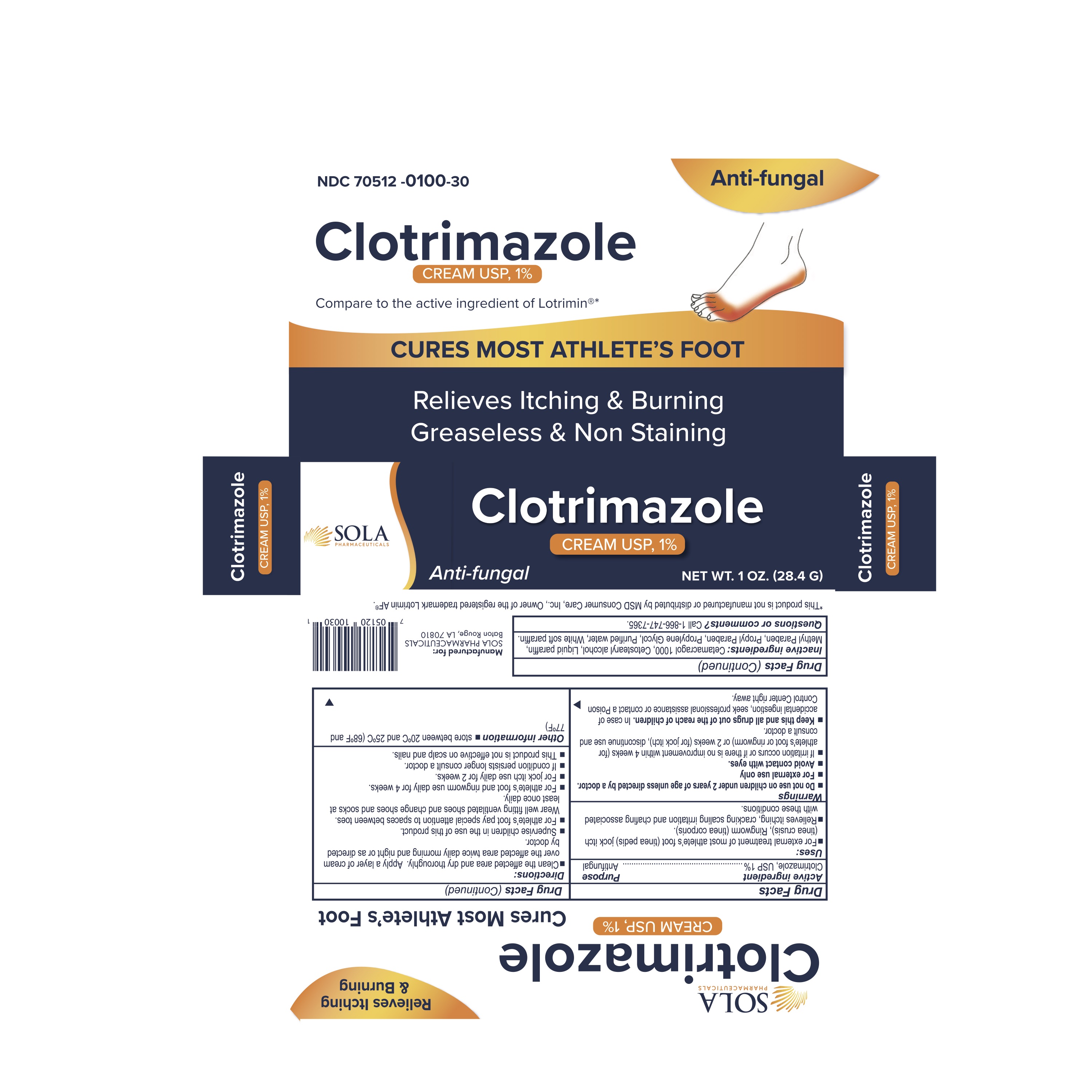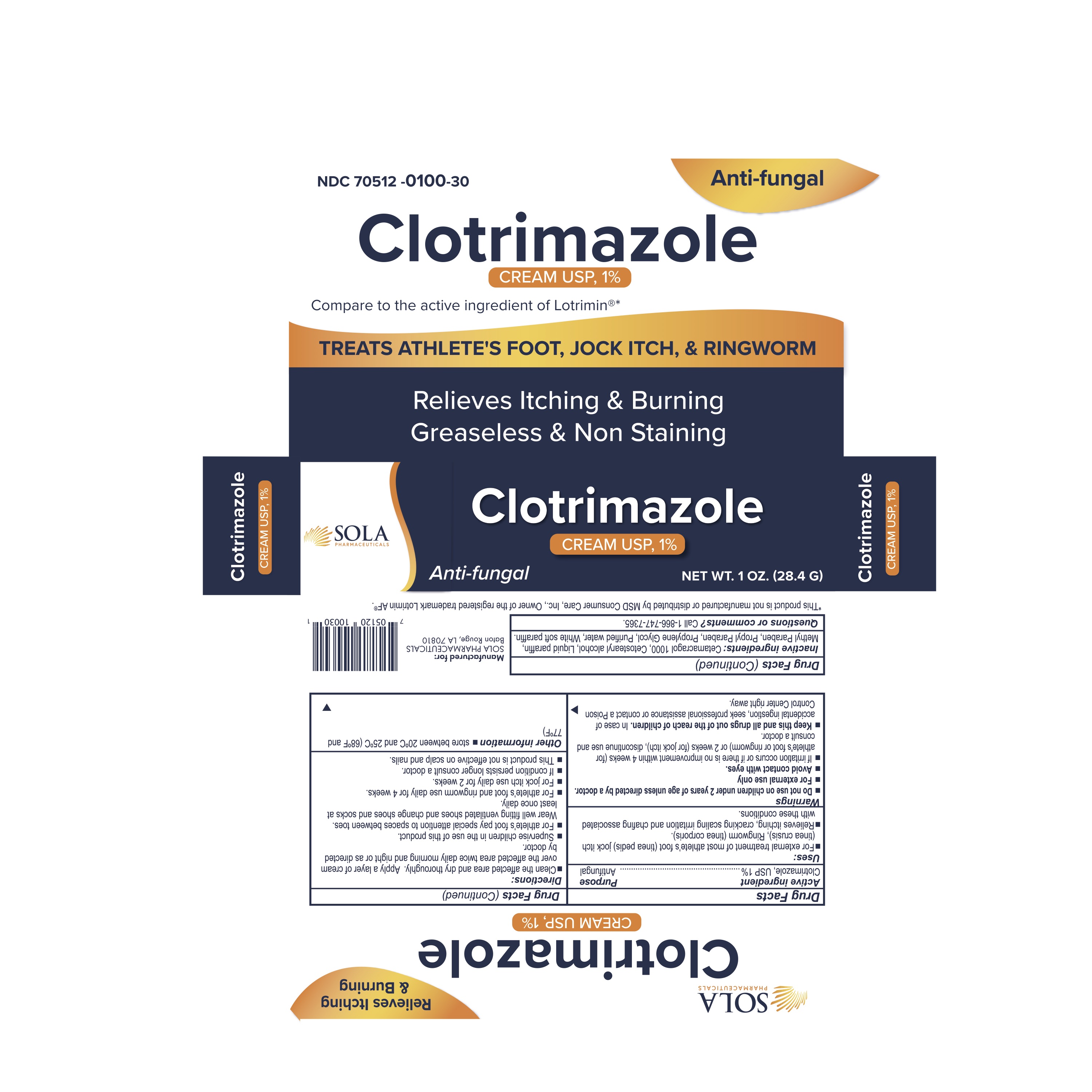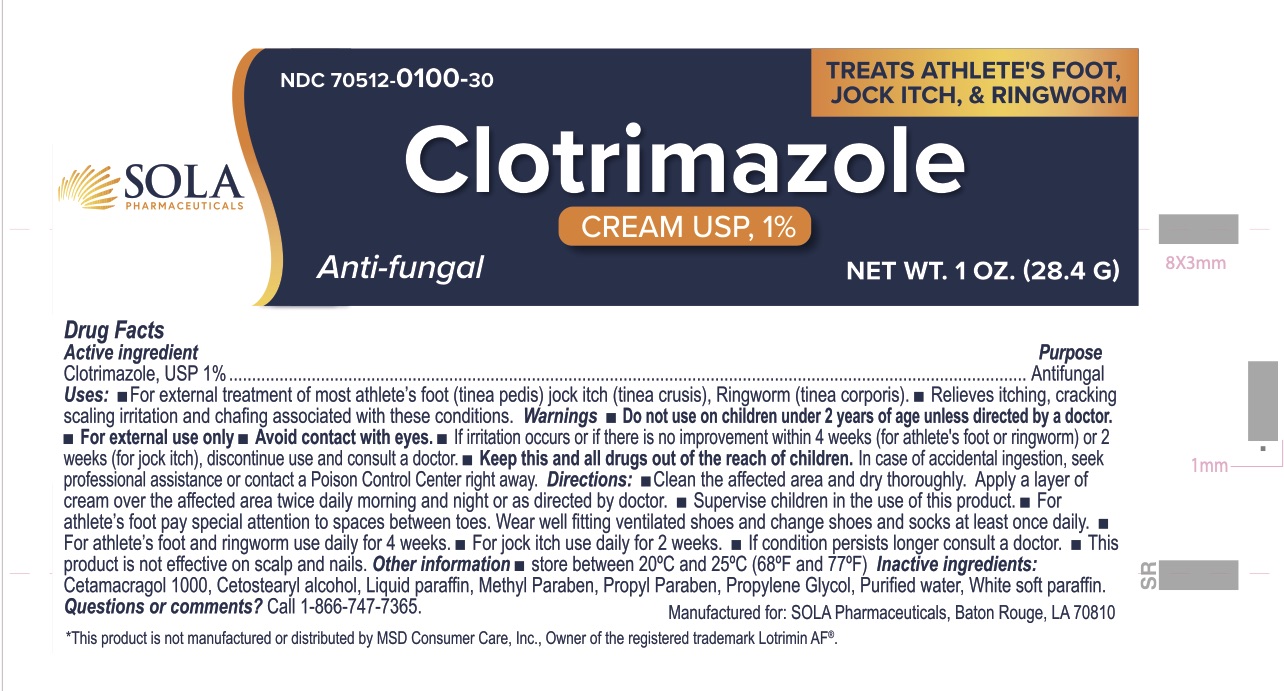 DRUG LABEL: Clotrimazole Cream 1%
NDC: 70512-100 | Form: CREAM
Manufacturer: SOLA Pharmaceuticals
Category: otc | Type: HUMAN OTC DRUG LABEL
Date: 20220705

ACTIVE INGREDIENTS: CLOTRIMAZOLE 10 mg/1 g
INACTIVE INGREDIENTS: MINERAL OIL; PROPYLPARABEN; WATER; CETETH-20; CETOSTEARYL ALCOHOL; PETROLATUM; PROPYLENE GLYCOL; METHYLPARABEN

Clotrimazole Cream 1% - Antifungal Cream

Active Ingredient

Clotrimazole 1%

Purpose

Antifungal

Usage

- For External treatment of most athlete's foot (tinea pedis), jock ithc (tinea crusis), ringworm (tinea corporis).
- Relieves itching, cracking scaling irritation and chafing associated with these conditions.

Warnings

Do not use on children under 2 years of age unless directed by a doctor.

For external use only.

Avoid contact with eyes.

If irritation occurs or if there is no improvement within 4 weeks (for athlete's foot or ringworm) or 2 weeks (for jock itch), discontinue use and consult a doctor.

Keep this and all drugs out of the reach of children. In case of accidental ingestion, seek professional assistance or contact a Poison Control Center right away.

KEEP OUT OF REACH OF CHILDREN

Keep this and all drugs our of the reach of children. In case of accidental ingestion, seek profesional assistance or contact a Poison Control Center right away.

Directions

- Clean the affected area and dry thoroughly. Apply a layer of cream over the affected area twice daily morning and night or as directed by doctor.
- Supervise children in the use of this product.
- For athlete's foot pay special attention to the spaces between toes. Wear well fitting ventilated shoes and change shoes and socks at least once daily.
- For athlete's foot and ringworm use daily for 4 weeks.
- For jock itch use daily for 2 weeks.
- If condition persist longer consult a doctor.
- This product is not effective on scalp or nails.

Inactive Ingredients

Cetomacragol 1000, Cetostearyl alcohol, Liquid paraffin, Methyl Paraben, Propyl paraben, Propylene glycol, Purified water, White soft paraffin.

Other Information

- Store between 20ºC and 25ºC (68ºF and 77ºF)

Questions or comments?

Call 1-866-747-7365

Package Display Panel

Questions or comments?

Call 1-866-747-7365

Manufactured for : SOLA Pharmaceuticals
Baton Rouge, LA 70810

Store in a dry, cool place

For Comments or Questions, call 866-747-7365

Clotrimazole 1% Cream
NDC 70512-100-30

Qty: 28.4g

NDC 70512-100-15

QTY 14.2